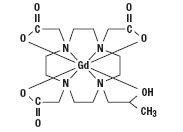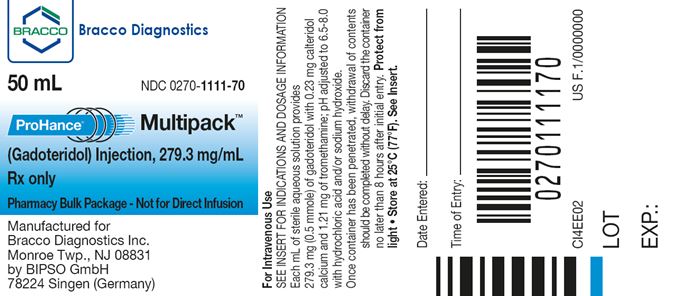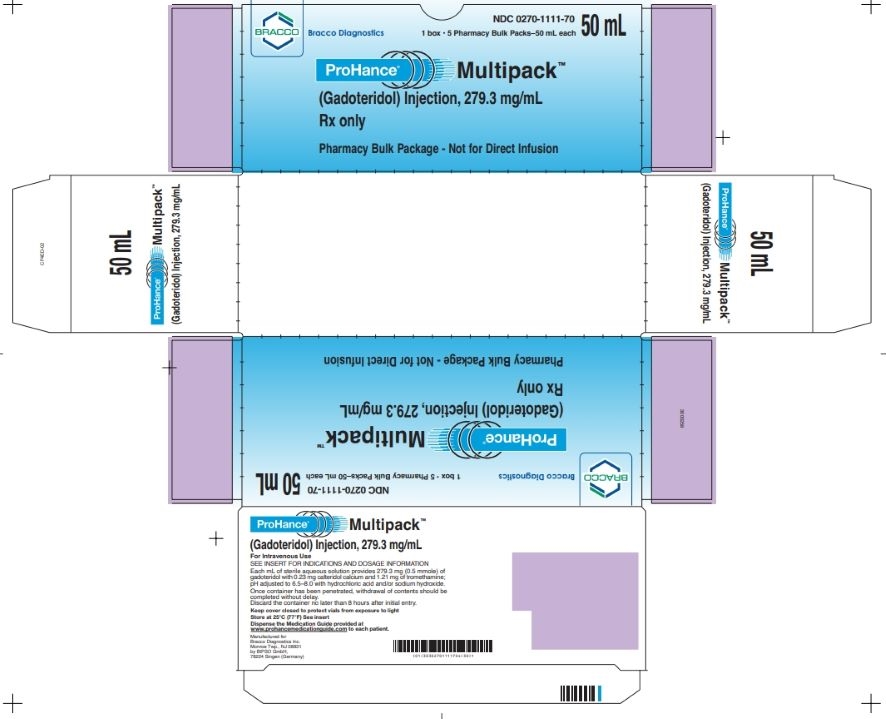 DRUG LABEL: ProHance
NDC: 0270-1111 | Form: INJECTION, SOLUTION
Manufacturer: Bracco Diagnostics Inc
Category: prescription | Type: HUMAN PRESCRIPTION DRUG LABEL
Date: 20250314

ACTIVE INGREDIENTS: gadoteridol 279.3 mg/1 mL
INACTIVE INGREDIENTS: calteridol calcium 0.23 mg/1 mL; tromethamine 1.21 mg/1 mL

HIGHLIGHTS OF PRESCRIBING INFORMATION

These highlights do not include all the information needed to use PROHANCE MULTIPACK safely and effectively. See full prescribing information for PROHANCE MULTIPACK.
PROHANCE MULTIPACK (gadoteridol injection), for intravenous use PHARMACY BULK PACKAGE -- NOT FOR DIRECT INFUSION
Initial U.S. Approval: 2003

WARNING: RISK ASSOCIATED WITH INTRATHECAL USE and NEPHROGENIC SYSTEMIC FIBROSIS

See full prescribing information for complete boxed warning

- Intrathecal administration of gadolinium based contrast agents (GBCAs) can cause serious adverse reactions including death, coma, encephalopathy, and seizures. ProHance is not approved for intrathecal use. (5.1)
- GBCAs increase the risk for nephrogenic systemic fibrosis (NSF) among patients with impaired elimination of the drugs. Avoid use of ProHance in these patients unless the diagnostic information is essential and not available with non-contrasted MRI or other modalities. NSF may result in fatal or debilitating systemic fibrosis affecting the skin, muscle and internal organs. The risk for NSF appears highest among patients with:
  - chronic, severe kidney disease (GFR less than 30 mL/min/1.73m^2), or
  - acute kidney injury
  Screen patients for acute kidney injury and other conditions that may reduce renal function. For patients at risk for chronically reduced renal function (e.g. age greater than 60 years, hypertension or diabetes), estimate the glomerular filtration rate (GFR) through laboratory testing (5.2).

1 INDICATIONS AND USAGE

ProHance Multipack is a gadolinium-based contrast agent indicated for magnetic resonance imaging (MRI) to visualize:

- lesions with disrupted blood brain barrier and/or abnormal vascularity in the brain (intracranial lesions), spine and associated tissues in adults and pediatric patients, including term neonates (1.1)
- lesions in the head and neck in adults (1.2)

2 DOSAGE AND ADMINISTRATION

- Dispense multiple single doses into separate sterile syringes for intravenous administration (2.3)
- Recommended dose in adult and pediatric patients is 0.2 mL/kg (0.1 mmol/kg) body weight administered as rapid intravenous infusion or bolus (2.1)
- Follow injection with a saline flush of at least 5 mL normal saline (2.1)

3 DOSAGE FORMS AND STRENGTHS

Injection: contains 279.3 mg/mL (0.5 mmol/mL) of gadoteridol supplied in a pharmacy bulk pack (2.3, 3, 16).

4 CONTRAINDICATIONS

Allergic or hypersensitivity reactions to ProHance (4).

5 WARNINGS AND PRECAUTIONS

- Hypersensitivity: anaphylactic/anaphylactoid reactions with cardiovascular, respiratory and cutaneous manifestations, ranging from mild to severe reactions including shock can occur. Monitor patients closely for need of emergency cardiorespiratory support (5.3).
- Gadolinium is retained for months or years in brain, bone, and other organs. (5.4)

6 ADVERSE REACTIONS

The most commonly reported adverse reactions are nausea and taste perversion with an incidence ≥ 0.9% (6.1)

To report SUSPECTED ADVERSE REACTIONS, Contact Bracco Diagnostics Inc. at 1-800-257-5181 or FDA at 1-800-FDA-1088 or www.fda.gov/medwatch

8 USE IN SPECIFIC POPULATIONS

Pregnancy: Use only if imaging is essential during pregnancy and cannot be delayed. (8.1)

FULL PRESCRIBING INFORMATION

WARNING: RISK ASSOCIATED WITH INTRATHECAL USE and NEPHROGENIC SYSTEMIC FIBROSIS

Risk Associated with Intrathecal Use
Intrathecal administration of gadolinium-based contrast agents (GBCAs) can cause serious adverse reactions including death, coma, encephalopathy, and seizures. ProHance is not approved for intrathecal use [see Warnings and Precautions (5.1)].

Nephrogenic Systemic Fibrosis
GBCAs increase the risk for nephrogenic systemic fibrosis (NSF) among patients with impaired elimination of the drugs. Avoid use of ProHance in these patients unless the diagnostic information is essential and not available with non-contrasted MRI or other modalities. NSF may result in fatal or debilitating systemic fibrosis affecting the skin, muscle and internal organs.

The risk for NSF appears highest among patients with:

- chronic, severe kidney disease (GFR less than 30 mL/min/1.73m^2), or
- acute kidney injury

Screen patients for acute kidney injury and other conditions that may reduce renal function. For patients at risk for chronically reduced renal function (e.g. age greater than 60 years, hypertension or diabetes), estimate the glomerular filtration rate (GFR) through laboratory testing.

For patients at highest risk for NSF, do not exceed the recommended ProHance dose and allow a sufficient period of time for elimination of the drug from the body prior to re-administration [see Warnings and Precautions (5.2)].

1 INDICATIONS AND USAGE

1.1 MRI of the Central Nervous System (CNS)

ProHance is indicated for magnetic resonance imaging (MRI) in adults and pediatric patients including term neonates to visualize lesions with disrupted blood brain barrier and/or abnormal vascularity in the brain (intracranial lesions), spine and associated tissues.

1.2 MRI of Extracranial/Extraspinal Tissues

ProHance is indicated for MRI in adults to visualize lesions in the head and neck.

2 DOSAGE AND ADMINISTRATION

2.1 Recommended Dose

The recommended dose for adult and pediatric patients, including term neonates, is 0.2 mL/kg (0.1 mmol/kg) administered as a rapid intravenous infusion (10 mL/min to 60 mL/min) or bolus (greater than 60 mL/min). Table 1 provides weight-adjusted recommended dose volumes.

Table 1: Recommended Volume of ProHance Injection by Body Weight
Body Weight (kg) | Volume to be Administered (mL)
2.5 | 0.5
5 | 1
10 | 2
20 | 4
30 | 6
40 | 8
50 | 10
60 | 12
70 | 14
80 | 16
90 | 18
100 | 20
110 | 22
120 | 24
130 | 26
140 | 28
150 | 30

MRI of the CNS in Adults:

- A supplementary dose of 0.4 mL/kg (0.2 mmol/kg) may be given up to 30 minutes after the first dose in adult patients with normal renal function suspected of having poorly visualized CNS lesions, in the presence of negative or equivocal scans
- The safety and efficacy of supplementary dosing have not been established in pediatric patients

2.2 Administration

- Visually inspect ProHance for particulate matter and discoloration prior to use
- Do not administer the solution if it is discolored or particulate matter is present
- Concurrent medications or parenteral nutrition should not be physically mixed with contrast agents and should not be administered in the same intravenous line because of the potential for chemical incompatibility
- Inject at least a 5 mL normal saline flush immediately after ProHance injection to ensure complete administration
- Imaging procedures should be completed within 1 hour

2.3 Directions for Proper Use of Pharmacy Bulk Package

NOT FOR DIRECT INFUSION
The pharmacy bulk package is used as a multiple dose container with an appropriate transfer device to fill empty sterile syringes. Use the following procedures when transferring ProHance from the pharmacy bulk package to individual syringes:

- Use of this product is restricted to a suitable work area, such as a laminar flow hood, utilizing aseptic technique
- Prior to entering the vial, remove the seal and cleanse the rubber closure with a suitable antiseptic agent
- The container closure may be penetrated only one time, utilizing a suitable transfer device or dispensing set that allows measured dispensing of the contents
- Once the pharmacy bulk package is punctured, it should not be removed from the aseptic work area during the entire period of use
- Withdrawal of container contents should be accomplished without delay. A maximum time of 8 hours from initial closure entry is permitted to complete fluid transfer operations
- Any unused contents must be discarded by 8 hours after initial puncture of the bulk package
- Once drawn into syringe, administer transferred agent promptly for single-dose administration

3 DOSAGE FORMS AND STRENGTHS

ProHance Multipack is supplied as a sterile, nonpyrogenic, and colorless to slightly yellow solution available in 50 mL and 100 mL pharmacy bulk packages for intravenous administration. Each mL contains 279.3 mg (0.5 mmol/mL) of gadoteridol for injection.

4 CONTRAINDICATIONS

ProHance is contraindicated in patients with known allergic or hypersensitivity reactions to ProHance [see Warnings and Precautions (5.3)].

5 WARNINGS AND PRECAUTIONS

5.1 Risk Associated with Intrathecal Use

Intrathecal administration of GBCAs can cause serious adverse reactions including death, coma, encephalopathy, and seizures. The safety and effectiveness of ProHance have not been established with intrathecal use. ProHance is not approved for intrathecal use [see Dosage and Administration (2.1)].

5.2 Nephrogenic Systemic Fibrosis

GBCAs increase the risk for nephrogenic systemic fibrosis (NSF) among patients with impaired elimination of the drugs. Avoid use of ProHance among these patients unless the diagnostic information is essential and not available with non-contrast MRI or other modalities. The GBCA-associated NSF risk appears highest for patients with chronic, severe kidney disease (GFR less than 30 mL/min/1.73m^2) as well as patients with acute kidney injury. The risk appears lower for patients with chronic, moderate kidney disease (GFR 30-59 mL/min/1.73m^2) and little, if any, for patients with chronic, mild kidney disease (GFR 60-89 mL/min/1.73m^2). NSF may result in fatal or debilitating fibrosis affecting the skin, muscle and internal organs. Report any diagnosis of NSF following ProHance Multipack administration to Bracco Diagnostics (1-800-257-5181) or FDA (1-800-FDA-1088 or www.fda.gov/medwatch).

Screen patients for acute kidney injury and other conditions that may reduce renal function. Features of acute kidney injury consist of rapid (over hours to days) and usually reversible decrease in kidney function, commonly in the setting of surgery, severe infection, injury or drug-induced kidney toxicity. Serum creatinine levels and estimated GFR may not reliably assess renal function in the setting of acute kidney injury. For patients at risk for chronically reduced renal function (for example, age greater than 60 years, diabetes mellitus or chronic hypertension), estimate the GFR through laboratory testing.

Among the factors that may increase the risk for NSF are repeated or higher than recommended doses of a GBCA and the degree of renal impairment at the time of exposure. Record the specific GBCA and the dose administered to a patient. For patients at highest risk for NSF, do not exceed the recommended ProHance dose and allow a sufficient period of time for elimination of the drug prior to re-administration. For patients receiving hemodialysis, physicians may consider the prompt initiation of hemodialysis following the administration of a GBCA in order to enhance the contrast agent’s Page 4 elimination. The usefulness of hemodialysis in the prevention of NSF is unknown [see Clinical Pharmacology (12)].

5.3 Hypersensitivity Reactions

Anaphylactic and anaphylactoid reactions have been reported, involving cardiovascular, respiratory, and/or cutaneous manifestations. Some patients experienced circulatory collapse and died. In most cases, initial symptoms occurred within minutes of ProHance administration and resolved with prompt emergency treatment.

Prior to ProHance administration, ensure the availability of trained personnel and medications to treat hypersensitivity reactions. Consider the risk for hypersensitivity reactions, especially in patients with a history of hypersensitivity reactions or a history of asthma or other allergic disorders. If such a reaction occurs, stop ProHance and immediately begin appropriate therapy. Observe patients for signs and symptoms of a hypersensitivity reaction during and for up to 2 hours after ProHance administration.

5.4 Gadolinium Retention

Gadolinium is retained for months or years in several organs. The highest concentrations (nanomoles per gram of tissue) have been identified in the bone, followed by other organs (e.g. brain, skin, kidney, liver, and spleen). The duration of retention also varies by tissue and is longest in bone. Linear GBCAs cause more retention than macrocyclic GBCAs. At equivalent doses, retention varies among the linear agents with Omniscan (gadodiamide) and Optimark (gadoversetamide) causing greater retention than other linear agents [Eovist (gadoxetate disodium), Magnevist (gadopentetate dimeglumine), MultiHance (gadobenate dimeglumine)]. Retention is lowest and similar among the macrocyclic GBCAs [Dotarem (gadoterate meglumine), Gadavist (gadobutrol), ProHance (gadoteridol)].

Consequences of gadolinium retention in the brain have not been established. Pathologic and clinical consequences of GBCA administration and retention in skin and other organs have been established in patients with impaired renal function [see Warnings and Precautions (5.2)]. There are rare reports of pathologic skin changes in patients with normal renal function. Adverse events involving multiple organ systems have been reported in patients with normal renal function without an established causal link to gadolinium retention [see Adverse Reactions (6.2)].

While clinical consequences of gadolinium retention have not been established in patients with normal renal function, certain patients might be at higher risk. These include patients requiring multiple lifetime doses, pregnant and pediatric patients, and patients with inflammatory conditions. Consider the retention characteristics of the agent when choosing a GBCA for these patients. Minimize repetitive GBCA imaging studies, particularly closely spaced studies when possible.

5.5 Acute Kidney Injury

In patients with chronically reduced renal function, acute kidney injury requiring dialysis has occurred with the use of GBCAs. The risk of acute kidney injury may increase with increasing dose of the contrast agent; administer the lowest dose necessary for adequate imaging.

6 ADVERSE REACTIONS

The following serious adverse reactions are discussed in greater detail in other sections of the prescribing information:

- Nephrogenic systemic fibrosis [see Boxed Warning and Warnings and Precautions (5.2)]
- Hypersensitivity reactions [see Contraindications (4) and Warnings and Precautions (5.3)]

6.1 Clinical Trials Experience

Because clinical trials are conducted under widely varying conditions, adverse reaction rates observed in the clinical trials of a drug cannot be directly compared to rates in the clinical trials of another drug and may not reflect the rates observed in practice.

The adverse events described in this section were observed in clinical trials involving 3174 subjects (including 2896 adults and 278 pediatric subjects ages 0 to 17 years) exposed to ProHance. Approximately 48% of the subjects were men and ethnic distribution was 78% Caucasian, 6% Black, 3% Hispanic, 6% Asian, and 2% other. In 5% of the subjects, race was not reported. Average age was 47 years (range from 1 day to 91 years) and the exposure ranged from 0.03 to 0.3 mmol/kg.

Overall, approximately 5.8% of subjects reported one or more adverse reactions during a follow-up period that ranged from 24 hours to 7 days after ProHance administration.

Table 2 lists adverse reactions that occurred in ≥ 0.4% subjects who received ProHance.
Table 2: More frequent adverse reactions in clinical trials
Reaction | Rate (%) N = 3174
Nausea | 1.4%
Dysgeusia | 0.9%
Headache | 0.7%
Dizziness | 0.4%
Urticaria | 0.4%

The following additional adverse events occurred in fewer than 0.4% of the subjects:
General disorders and administration site conditions: | Asthenia; chest discomfort, facial edema, feeling hot, injection site coldness, injection site erythema, injection site pain, injection site warmth, pain, pyrexia
Cardiac: | Angina pectoris, palpitations, atrio-ventricular block first degree
Ear and labyrinth disorders: | Ear discomfort, tinnitus
Eye disorders: | Eye pruritis, lacrimation increased
Gastrointestinal disorders: | Abdominal discomfort, abdominal pain, diarrhea, dry mouth, gingival pain, oral pruritis, swollen tongue, vomiting
Infections and infestations: | Gingivitis, rhinitis
Investigations: | Alanine aminotransferase increased, aspartate aminotransferase increased, blood chloride increased, blood pressure immeasurable, blood urea decreased, hemoglobin decreased, heart rate increased
Metabolism and nutrition disorders: | Decreased appetite, hypoglycemia
Musculoskeletal and connective tissue disorders: | Back pain, musculoskeletal stiffness
Nervous system disorders: | Formication, hypoesthesia, hypokinesia, lethargy, loss of consciousness, migraine, paresthesia, presyncope, seizure, syncope, taste disorder
Psychiatric disorders: | Anxiety, mental status changes
Respiratory, thoracic and mediastinal disorders: | Cough, dry throat, dyspnea, nasal discomfort, throat irritation
Skin and subcutaneous tissue disorders: | Hyperhidrosis, pruritis, rash, rash morbilliform
Vascular disorders: | Flushing, hypotension, peripheral coldness, vascular rupture, vasodilatation, vasospasm

6.2 Postmarketing Experience

The following adverse reactions have been identified during post approval use of ProHance or other GBCAs that were not observed in the clinical trials. Because these reactions are reported voluntarily from a population of uncertain size, it is not always possible to reliably estimate their frequency or establish a causal relationship to drug exposure.

The following adverse drug reactions have also been reported:
General Disorders and Administration Site Conditions: | Adverse events with variable onset and duration have been reported after GBCA administration [see Warnings and Precautions (5.4)]. These include fatigue, asthenia, pain syndromes, and heterogeneous clusters of symptoms in the neurological, cutaneous, and musculoskeletal systems.
Cardiac disorders: | Cardiac arrest, bradycardia, hypertension
Gastrointestinal disorders: | Acute pancreatitis with onset within 48 hours after GBCA administration
Immune system disorders: | Hypersensitivity/anaphylactoid reactions including cardiac arrest, cyanosis, pharyngeal edema, laryngospasm, bronchospasm, angioedema, cough, sneezing, conjunctivitis, eyelid edema, hyperhidrosis, urticaria [see Warnings and Precautions (5.3)].
Nervous system disorders: | Coma, loss of consciousness, vasovagal reaction, tremor
Respiratory, thoracic and mediastinal disorders: | Respiratory arrest, acute respiratory distress syndrome, pulmonary edema
Renal and urinary system disorders: | Acute renal failure *
* Cases of acute renal failure have been reported in patients with pre-existing severe renal impairment.

8 USE IN SPECIFIC POPULATIONS

8.1 Pregnancy

Risk Summary
GBCAs cross the placenta and result in fetal exposure and gadolinium retention. The human data on the association between GBCAs and adverse fetal outcomes are limited and inconclusive (see Data). Because of the potential risks of gadolinium to the fetus, use ProHance only if imaging is essential during pregnancy and cannot be delayed.

In animal reproduction studies in rats, gadoteridol doubled the incidence of post-implantation loss at up to 16 times the recommended human dose (RHD). There were no adverse developmental effects observed in rabbits with intravenous administration of gadoteridol during organogenesis at doses up to 19 times the recommended human dose of 0.1 mmol/kg (see Data).

The estimated background risk of major birth defects and miscarriage for the indicated population is unknown. All pregnancies have a background risk of birth defect, loss, or other adverse outcomes. In the U.S. general population, the estimated background risk of major birth defects and miscarriage in clinically recognized pregnancies is 2 to 4% and is 15 to 20%, respectively.

Data
Human Data
Contrast agent is visualized in the placenta and fetal tissues after maternal GBCA administration. Cohort studies and case reports on exposure to GBCAs during pregnancy have not reported a clear association between GBCAs and adverse effects in the exposed neonates. However, a retrospective cohort study, comparing pregnant women who had a GBCA MRI to pregnant women who did not have an MRI, reported a higher occurrence of stillbirths and neonatal deaths in the group receiving GBCA MRI. Limitations of this study include a lack of comparison with non-contrast MRI and lack of information about the maternal indication for MRI.

Animal Data
Gadolinium Retention
GBCAs administered to pregnant non-human primates (0.1 mmol/kg on gestational days 85 and 135) result in measurable gadolinium concentration in the offspring in bone, brain, skin, liver, kidney, and spleen for at least 7 months. GBCAs administered to pregnant mice (2 mmol/kg daily on gestational days 16 through 19) result in measurable gadolinium concentrations in the pups in bone, brain, kidney, liver, blood, muscle, and spleen at one-month postnatal age.

Reproductive Toxicology
Gadoteridol was administered in intravenous doses of 0, 0.375, 1.5, 6.0, and 10 mmol/kg/day [0.6, 2.4, 9.7, and 16 times the recommended human dose (RHD) based on body surface area (BSA)] to female rats from gestational day (GD)6 until GD17. Gadoteridol at 10 mmol/kg/day for 12 days during gestation doubled the incidence of post-implantation loss. When rats were administered 6.0 or 10.0 mmol/kg/day for 12 days, an increase in spontaneous locomotor activity was observed in the offspring. Pregnant rabbits were administered gadoteridol in intravenous doses of 0, 0.4, 1.5, and 6 mmol/kg/day (1.3, 4.8, and 19.4 times the RHD based on BSA) from GD6 to GD18. Gadoteridol increased the incidence of spontaneous abortion and early delivery in rabbits administered 6 mmol/kg/day for 13 days during gestation.

8.2 Lactation

Risk Summary
There are no data on the presence of gadoteridol in human milk, the effects on the breastfed infant, or the effects on milk production. However, published lactation data on other GBCAs indicate that 0.01 to 0.04% of the maternal gadolinium dose is present in breast milk and there is limited GBCA gastrointestinal absorption in the breast-fed infant. Gadoteridol is present in rat milk (see Data). The developmental and health benefits of breastfeeding should be considered along with the mother’s clinical need for ProHance and any potential adverse effects on the breastfed infant from ProHance or from the underlying maternal condition.

Data
ProHance excretion in the milk of lactating rats was evaluated at 30 minutes, 6 and 24 hours after intravenous administration of 0.1 mmol/kg of ^153Gd-gadoteridol to nursing mothers. Small amounts of compound were found in milk immediately after injection (0.14% of the ID), with the amount declining to a low level 24 hours after injection (<0.01% of the ID).

8.4 Pediatric Use

The safety and effectiveness of ProHance have been established for use with MRI to visualize lesions with abnormal blood brain barrier or abnormal vascularity of the brain, spine, and associated tissues in pediatric patients from birth, including term neonates, to 17 years of age. Pediatric use is based on evidence of effectiveness in adults and in 103 pediatric patients 2 years of age and older, in addition to experience in 125 pediatric patients birth to less than 2 years of age that supported extrapolation from adult data [see Clinical Studies (14)]. Adverse reactions in pediatric patients were similar to those reported in adults [see Adverse Reactions (6.1)].

The safety and efficacy of > 0.1 mmol/kg, and sequential and/or repeat procedures have not been studied in pediatric patients [see Indications and Usage (1) and Dosage and Administration (2)].

No case of NSF associated with ProHance or any other GBCA has been identified in pediatric patients ages 6 years and younger. Pharmacokinetic studies suggest that weight normalized clearance of ProHance is similar in pediatric patients and adults, including pediatric patients age younger than 2 years. Normal estimated GFR (eGFR) is around 30 mL/min/1.73m^2 at birth and increases to mature levels around 1 year of age, reflecting growth in both glomerular function and relative body surface area. Clinical studies in pediatric patients younger than 1 year of age have been conducted in patients with the following minimum eGRF; 59.37 mL/min/1.73m^2 (age just after birth to < 30 days), 118.84 mL/min/1.73m^2 (age 30 days to < 6 months), 140.44 mL/min/1.73m^2 (age 6 to 12 months).

8.5 Geriatric Use

Of the total number of 2673 adult subjects in clinical studies of ProHance, 22% were 65 and over. No overall differences in safety were observed between these elderly subjects and the younger subjects.

ProHance is known to be substantially excreted by the kidneys, and the risk of toxic reactions from ProHance may be greater in patients with impaired renal function. Because elderly patients are more likely to have decreased renal function, it may be useful to monitor renal function.

8.6 Renal Impairment

No ProHance dosage adjustment is recommended for patients with renal impairment. Gadoteridol can be removed from the body by hemodialysis [see Warning and Precautions (5.2) and Clinical Pharmacology (12.3)].

10 OVERDOSAGE

Clinical consequences of overdose with ProHance have not been reported. The safety of ProHance has been tested in clinical studies using doses up to 0.3 mmol/kg and no clinical consequences related to increasing dose have been observed to date. ProHance can be removed by hemodialysis [see Use in Specific Populations (8.6) and Clinical Pharmacology (12.3)].

11 DESCRIPTION

ProHance, a gadolinium-based paramagnetic MRI contrast agent, is a colorless to slightly yellow aqueous, sterile, nonpyrogenic injectable solution. Each mL contains 279.3 mg (0.5 mmol/mL) gadoteridol, 0.23 mg calteridol calcium, 1.21 mg tromethamine and water for injection; pH adjusted with hydrochloric acid and/or sodium hydroxide. ProHance contains no antimicrobial preservative.

Gadoteridol is the gadolinium complex of 10-(2-hydroxy-propyl)-1,4,7,10-tetraazacyclododecane-1,4,7- triacetic acid with a molecular weight of 558.7, an empirical formula of C17H29N4O7Gd and has the following structural formula:

ProHance has a pH of 6.5 to 8.0. Pertinent physiochemical parameters are provided below:

Osmolality | 630 mOsmol/kg water at 37 °C
Viscosity | 1.3 cP at 37 °C
Density | 1.137 g/mL at 25 °C

ProHance has an osmolality that is 2.2 times that of plasma (285 mOsmol/kg water) and is hypertonic under conditions of use.

12 CLINICAL PHARMACOLOGY

12.1 Mechanism of Action

Gadoteridol is a paramagnetic agent and, as such, develops a magnetic moment when placed in a magnetic field. The relatively large magnetic moment produced by the paramagnetic agent results in a relatively large local magnetic field, which can enhance the relaxation rates of water protons in the vicinity of the paramagnetic agent.

In MRI, visualization of normal and pathologic brain tissue depends, in part, on variations in the radiofrequency signal intensity that occur with: 1) differences in proton density; 2) differences of the spin-lattice or longitudinal relaxation times (T1); and 3) differences in the spin-spin or transverse relaxation time (T2). When placed in a magnetic field, gadoteridol decreases T1 relaxation times in the target tissues. At recommended doses, the effect is observed with greatest sensitivity in the T1-weighted sequences.

12.2 Pharmacodynamics

Gadoteridol affects proton relaxation times and consequently the MR signal. Signal intensity is affected by the dose and relaxivity of the gadoteridol molecule. Consistently, for all gadolinium based contrast agents, the relaxivity of gadoteridol decreases with the increase of the magnetic field strength used in clinical MRI (0.2 – 3.0T).

Disruption of the blood-brain barrier or abnormal vascularity allows accumulation of gadoteridol in lesions such as neoplasms, abscesses, and subacute infarcts. The pharmacokinetics of gadoteridol in various lesions is not known.

12.3 Pharmacokinetics

The pharmacokinetics of intravenously administered gadoteridol in normal subjects conforms to a two-compartment open model.

Distribution
After intravenous administration, gadoteridol is rapidly distributed in the extracellular space. The plasma distribution volume (mean ± SD) for the non-renally impaired adults was 0.205 ± 0.025 L/kg. It is unknown if protein binding of gadoteridol occurs in vivo.

Following GBCA administration, gadolinium is present for months or years in brain, bone, skin, and other organs [see Warnings and Precautions (5.4)].

Metabolism
It is unknown if biotransformation or decomposition of gadoteridol occur in vivo.

Elimination
Gadoteridol is eliminated unchanged via the kidneys. The elimination half-life (mean ± SD) is about 1.57 ± 0.08 hours. Within 24 hours post-injection, 94.4 ± 4.8% of the dose is excreted in the urine. The renal and plasma clearance rates (1.41 ± 0.33 mL/ min/kg and 1.50 ± 0.35 mL/ min/kg, respectively) of gadoteridol are essentially identical, indicating no alteration in elimination kinetics on passage through the kidneys and that the drug is essentially cleared through the kidney. The volume of distribution (204 ± 58 mL/kg) is equal to that of extracellular water, and clearance is similar to that of substances which are subject to glomerular filtration.

Specific Populations
Gender
Gender has no clinically relevant effect on the pharmacokinetics of gadoteridol.

Geriatric
There were 7 elderly subjects receiving 0.1 (n = 3) and 0.3 mmol/kg (n = 4) dose of ProHance. The clearance was slightly lower in elderly subjects as compared to non-elderly subjects. [see Use in Specific Populations (8.5)].

Pediatric
A population pharmacokinetic analysis incorporated data from 79 subjects, 45 males and 34 females. Among 79 subjects, 41 were healthy subjects including 28 pediatric subjects between 5 years and 15 years of age. The pediatric subjects received a single intravenous dose of 0.1 mmol/kg of ProHance. From population PK model, the mean Cmax was 0.66 ± 0.21 mmol/L in pediatric subjects 2 years to 6 years of age, 0.58 ± 0.06 mmol/L in pediatric subjects 6 years to 12 years of age, and 0.68 ± 0.12 mmol/L in adolescent subjects older than 12 years. The mean AUC 0-∞ was 0.74 ± 0.20 mmol/L⋅h in pediatric subjects 2 years to 6 years of age, 0.74 ± 0.09 mmol/L⋅h in pediatric subjects 6 years to 12 years of age, and 0.98 ± 0.09 mmol/L⋅h in adolescent subjects older than 12 years of age. The mean distribution half- life (t1/2,alpha) was 0.14 ± 0.04 hours in pediatric subjects 2 years to 6 years of age, 0.18 ± 0.07 hours in pediatric subjects 6 years to 12 years of age, and 0.20 ± 0.07 hours in adolescent subjects older than 12 years of age. The mean elimination half-life (t1/2,beta) was 1.32 ± 0.006 hours in pediatric subjects 2 years to 6 years, 1.32 ± 0.07 hours in pediatric subjects 6 years to 12 years of age, and 1.61 ± 0.19 hours in adolescent subjects older than 12 years of age. There was no significant gender-related difference in the pharmacokinetic parameters in the pediatric patients. Over 80% of the dose was recovered in urine for pediatric subjects after 10 hours. Pharmacokinetic simulations indicate similar half-life, AUC, and Cmax values for ProHance in pediatric subjects less than 2 years of age when compared to those reported for adults; no age-based dose adjustment is necessary for this pediatric population.

Renal Impairment
In patients with impaired renal function, the serum half-life of gadoteridol is prolonged. After intravenous injection of 0.1 mmol/kg, the elimination half-life of gadoteridol was 10.65 ± 0.60 hours in mild to moderately impaired patients (creatinine clearance 30 to 60 mL/min) and 9.10±0.26 hours in severely impaired patients not on dialysis (creatinine clearance 10 to 30 mL/min). The mean serum clearance of gadoteridol in patients with normal renal function was 116.14 ± 26.77 mL/min, compared to 37.2 ± 16.4 mL/min in patients with mild to moderate renal impairment and 16.0 ± 3.0 mL/min in patients with severe renal impairment.

In patients with moderately and severely impaired renal function about 97% and 76% of the administered dose was recovered in the urine within 7 days and 14 days, respectively.

For patients receiving hemodialysis, physicians may consider the prompt initiation of hemodialysis following the administration of ProHance in order to enhance the contrast agent’s elimination. Seventy- two percent (72%) of gadoteridol is removed from the body after the first dialysis, 91% after the second dialysis, and 98% after the third dialysis session. [See Warnings and Precautions (5.2) and Use in Specific Populations (8.6).]

13 NONCLINICAL TOXICOLOGY

13.1 Carcinogenesis, Mutagenesis, Impairment of Fertility

No animal studies have been performed to evaluate the carcinogenic potential of gadoteridol.

No changes in reproductive performance and outcome of pregnancy were caused in rats and rabbits by daily intravenous administration of ProHance to parent animals before and during gestation up to 1.5 mmol/kg/day (15 times the recommended human dose).

Gadoteridol did not demonstrate genotoxic activity in: bacterial reverse mutation assays using Salmonella typhimurium and Escherichia coli; a mouse lymphoma forward mutation assay; an in vitro cytogenetic assay measuring chromosomal aberration frequencies in Chinese hamster ovary cells; and an in vivo mouse micronucleus assay at intravenous doses up to 5.0 mmol/kg.

14 CLINICAL STUDIES

14.1 MRI of the CNS

ProHance was evaluated in two multicenter trials of 310 evaluable patients suspected of having neurological pathology. After the administration of ProHance 0.1 mmol/kg IV, the results were similar to those described below [see Clinical Studies (14.2)].

In another multicenter study of 49 evaluable adult patients with known intracranial tumor with high suspicion of having cerebral metastases, two doses of ProHance were administered. First ProHance 0.1 mmol/kg was injected followed 30 minutes later with 0.2 mmol/kg. In comparison to the 0.1 mmol/kg dose alone, the addition of the 0.2 mmol/kg dose improved visualization in 67% and improved border definition in 56% of patients. In comparison to non-contrast MRI, the number of lesions after 0.1 mmol/kg increased in 34% of patients. After ProHance 0.2 mmol/kg, this increased to 44%.

Pediatric Patients
ProHance was evaluated in a multicenter study of 103 patients undergoing brain or spine MRI. Among these patients, the age range was 2 to 20 years; 54 were between 2 and 12 years of age; 74% were Caucasian, 11% Black, 12% Hispanic, 2% Asian, and 2% other. ProHance was given in one single 0.1 mmol/kg dose. Repeat dosing was not studied. The results of the non-contrast and ProHance MRI scans were compared. In this database, MRI enhancement was noted in approximately 60% of the scans and additional diagnostic information in 30 to 95% of the scans.

A prospectively planned study of 125 pediatric patients younger than 2 years of age retrospectively selected was performed. These patients (70 boys and 55 girls) had an age range of 1 day to 24 months old; 17 were less than 1 month of age, 40 were between 1 month and 6 months of age, 29 were between 6 months and 12 months of age, and 39 were between 12 months and 24 months of age; 56% were Caucasian, 25% Black, 5% Asian, and 14% other. ProHance was given in one single 0.1 mmol/kg dose. Repeat dosing was not studied. Three independent, blinded readers evaluated pre-contrast MRI image sets and paired pre-plus-post-contrast MRI image sets using ProHance and rated the images according to three co-primary visualization endpoints: lesion border delineation, visualization of lesion internal morphology, and lesion contrast enhancement. All three blinded readers reported improvement in the paired image sets for each of the three co-primary endpoints.

14.2 MRI of the Head and Neck

ProHance was evaluated in two blinded read studies in a total of 133 adults who had an indication for head and neck extracranial or extraspinal MRI. These 133 adults (74 men, 59 women) had a mean age of 53 with a range of 19 to 76 years. Of these patients, 85% were Caucasian, 13% Black, 2% Asian, and less than 1% other. The results of the non-contrast and contrast MRI scans were compared. Approximately 75-82% of the scans were enhanced, 45-48% of the scans provided additional diagnostic information, and 8-25% of the diagnoses were changed. The relevance of the findings to disease sensitivity and specificity has not been fully evaluated.

16 HOW SUPPLIED/STORAGE AND HANDLING

How Supplied
ProHance Multipack is supplied as a sterile, nonpyrogenic, and colorless to slightly yellow solution containing 279.3 mg/mL (0.5 mmol/mL) of gadoteridol in rubber stoppered vials. ProHance Multipack is supplied in boxes of five 50 mL pharmacy bulk packages (NDC 0270-1111-70) and boxes of five 100 mL pharmacy bulk packages (NDC-0270-1111-85).

Storage and Handling
Store at 25°C (77° F). Excursions permitted to 15°C to 30°C (59°F to 86°F) [See USP Controlled Room Temperature]. Protect from light. DO NOT FREEZE. Should freezing occur in the vial, ProHance Multipack should be brought to room temperature before use. If allowed to stand at room temperature for a minimum of 60 minutes, ProHance Multipack should return to a clear, colorless to slightly yellow solution. Before use, examine the product to assure that all solids are redissolved and that the container and closure have not been damaged. Should solids persist, discard vial.

17 PATIENT COUNSELING INFORMATION

Medication Guide

- Advise the patient to read the FDA-approved patient labeling (Medication Guide) found at www.prohancemedicationguide.com.

Nephrogenic Systemic Fibrosis
Instruct patients to inform their physician if they:

- have a history of kidney disease
- have recently received a GBCA

GBCAs increase the risk for NSF in patients with impaired elimination of the drugs. To counsel patients at risk for NSF:

- describe the clinical manifestations of NSF
- describe procedures to screen for the detection of renal impairment

Instruct patients to contact their physician if they develop signs or symptoms of NSF following ProHance administration, such as burning, itching, swelling, scaling, hardening and tightening of the skin; red or dark patches on the skin; stiffness in joints with trouble moving, bending or straightening the arms, hands, legs or feet; pain in the hip bones or ribs; or muscle weakness.

General Precautions

- Pregnancy: Advise a pregnant woman of the potential risk of fetal exposure to ProHance [see Use in Specific Populations (8.1)]
- Gadolinium retention: Advise patients that gadolinium is retained for months or years in brain, bone, skin, and other organs in patients with normal renal function. The clinical consequences of retention are unknown. Retention depends on multiple factors and is greater following administration of linear GBCAs than following administration of macrocyclic GBCAs [see Warnings and Precautions (5.4)].

Manufactured for:
Bracco Diagnostics Inc.
Princeton, NJ 08540

By BIPSO GmbH
78224 Singen (Germany)

March 2025

CL4EF-14

MEDICATION GUIDE
PROHANCE® (prō-ˈhan(t)s)
(Gadoteridol injection)
for intravenous use

What is the most important information I should know about PROHANCE?

- GBCAs like PROHANCE may cause serious side effects including death, coma, encephalopathy, and seizures when it is given intrathecally (injection given into the spinal canal). It is not known if PROHANCE is safe and effective with intrathecal use. PROHANCE is not approved for this use.
- PROHANCE contains a metal called gadolinium. Small amounts of gadolinium can stay in your body including the brain, bones, skin and other parts of your body for a long time (several months to years).
- It is not known how gadolinium may affect you, but so far, studies have not found harmful effects in patients with normal kidneys.
- Rarely, patients have reported pains, tiredness, and skin, muscle or bone ailments for a long time, but these symptoms have not been directly linked to gadolinium.
- There are different GBCAs that can be used for your MRI exam. The amount of gadolinium that stays in the body is different for different gadolinium medicines. Gadolinium stays in the body more after Omniscan or Optimark than after Eovist, Magnevist, or MultiHance. Gadolinium stays in the body the least after Dotarem, Gadavist, or ProHance.
- People who get many doses of gadolinium medicines, women who are pregnant and young children may be at increased risk from gadolinium staying in the body.
- Some people with kidney problems who get gadolinium medicines can develop a condition with severe thickening of the skin, muscles and other organs in the body (nephrogenic systemic fibrosis). Your healthcare provider should screen you to see how well your kidneys are working before you receive PROHANCE.

What is PROHANCE?

- PROHANCE is a prescription medicine called a gadolinium-based contrast agent (GBCA). PROHANCE, like other GBCAs, is used with a magnetic resonance imaging (MRI) scanner.
- An MRI exam with a GBCA, including PROHANCE, helps your doctor to see problems better than an MRI exam without a GBCA.
- Your doctor has reviewed your medical records and has determined that you would benefit from using a GBCA with your MRI exam.

Do not receive PROHANCE if you have had a severe allergic reaction to PROHANCE.

Before receiving PROHANCE, tell your healthcare provider about all your medical conditions, including if you:

- have had any MRI procedures in the past where you received a GBCA. Your healthcare provider may ask you for more information including the dates of these MRI procedures.
- are pregnant or plan to become pregnant. It is not known if PROHANCE can harm your unborn baby. Talk to your healthcare provider about the possible risks to an unborn baby if a GBCA such as PROHANCE is received during pregnancy
- have kidney problems, diabetes, or high blood pressure
- have had an allergic reaction to dyes (contrast agents) including GBCAs

What are the possible side effects of PROHANCE?

- See “What is the most important information I should know about PROHANCE?”
- Allergic reactions. PROHANCE can cause allergic reactions that can sometimes be serious. Your healthcare provider will monitor you closely for symptoms of an allergic reaction.

The most common side effects of PROHANCE include: nausea, distortion of the sense of taste, and headache.
These are not all the possible side effects of PROHANCE.
Call your doctor for medical advice about side effects. You may report side effects to FDA at 1-800-FDA-1088.

General information about the safe and effective use of PROHANCE.
Medicines are sometimes prescribed for purposes other than those listed in a Medication Guide. You can ask your healthcare provider for information about PROHANCE that is written for health professionals.

What are the ingredients in PROHANCE?
Active ingredient: gadoteridol
Inactive ingredients: calteridol calcium, tromethamine
Manufactured by: BIPSO GmbH-78224 Singen (Germany)
Manufactured for: Bracco Diagnostics Inc., Princeton, NJ 08540
For more information, go to www.imaging.bracco.com or call 1-800-257-5181.

This Medication Guide has been approved by the U.S. Food and Drug Administration

Revised: 03/2025

ProHance 50mL Label
NDC: 0270-1111-70

PACKAGE LABEL

ProHance 50mL Carton
NDC: 0270-1111-70